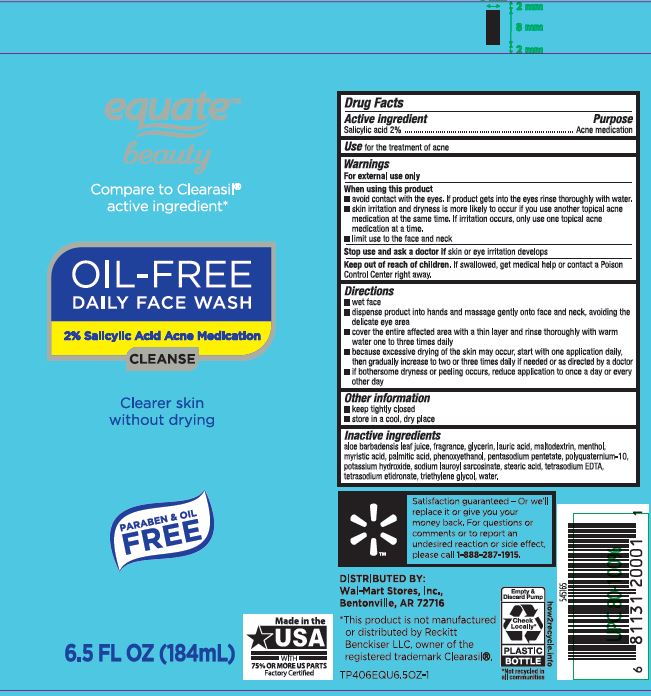 DRUG LABEL: Oil Free Daily Face
NDC: 79903-208 | Form: LIQUID
Manufacturer: Walmart
Category: otc | Type: HUMAN OTC DRUG LABEL
Date: 20260120

ACTIVE INGREDIENTS: SALICYLIC ACID 2 g/100 mL
INACTIVE INGREDIENTS: WATER; POTASSIUM HYDROXIDE; PALMITIC ACID; MENTHOL; POLYQUATERNIUM-10 (1000 MPA.S AT 2%); LAURIC ACID; ETIDRONATE TETRASODIUM; PHENOXYETHANOL; SODIUM BENZOATE; POTASSIUM SORBATE; EDETATE SODIUM; PENTASODIUM PENTETATE; SODIUM LAUROYL SARCOSINATE; STEARIC ACID; ALOE; MALTODEXTRIN; GLYCERIN; MYRISTIC ACID; TRIETHYLENE GLYCOL

OIL-FREE DAILY FACE WASH (acne)

Active Ingreient Purpose

Salicylic acid 2% ................................ Acne medication

Use

for the treatment of acne

When using this product

avoid contact with the eyes. If product gets into the eyes rinse thoroughly w􀃰h water.
skin irritation and dryness is more likely to occur if you use another topical acne medication at the same time. If irritation occurs, only use one topical acne medication at a time.

limit use to the face and neck

Stop use and ask a doctor if

skin or eye irritation develops

Keep out of reach of children.

If swallowed, get medical help or contact a Poison

Directions

wet face
dispense product into hands and massage gently onto face and neck, avoiding the delicate eye area
cover the entire affected area with a thin layer and rinse thoroughly with warm water one to three times daily
because excessive drying of the skin may occur, start with one application daily, then gradually increase to two or three times daily if needed or as directed by a doctor
if bothersome dryness or peeling occurs, reduce application to once a day or every other day

Other information

keep tightly closed
store in a cool, dry place

Inactive ingredients

aloe barbadensis leaf juice, fragrance, glycerin, lauric acid, maltodextrin, menthol,
myristic acid, palmitic acid, phenoxyethanol, pentasodium pentetate, polyquaternium-10,
potassium hydroxide, sodium lauroyl sarcosinate, stearic acid, tetrasodium EDTA,
tetrasodium etidronate, triethylene glycol, water.